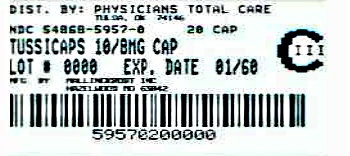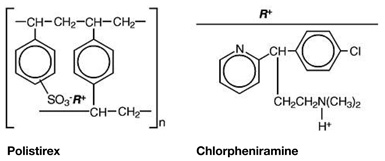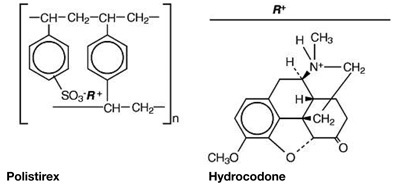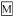 DRUG LABEL: TUSSICAPS
NDC: 54868-5957 | Form: CAPSULE, EXTENDED RELEASE
Manufacturer: Physicians Total Care, Inc.
Category: prescription | Type: HUMAN PRESCRIPTION DRUG LABEL 
Date: 20120608
DEA Schedule: CIII

ACTIVE INGREDIENTS: HYDROCODONE BITARTRATE 10 mg/1 1; CHLORPHENIRAMINE MALEATE 8 mg/1 1
INACTIVE INGREDIENTS: BUTYL ALCOHOL; GELATIN; FERROSOFERRIC OXIDE; ISOPROPYL ALCOHOL; CELLULOSE, MICROCRYSTALLINE; PROPYLENE GLYCOL; WATER; SHELLAC; AMMONIA; TITANIUM DIOXIDE; D&C YELLOW NO. 10; ALUMINUM OXIDE; FD&C BLUE NO. 1; FD&C BLUE NO. 2; INDIGOTINDISULFONATE SODIUM; FD&C RED NO. 40; ALCOHOL; METHYL ALCOHOL 

TussiCaps®
(Hydrocodone Polistirex and Chlorpheniramine Polistirex)
Extended-Release Capsules
CIII
Rx only

DESCRIPTION

Each full-strength TussiCaps® (hydrocodone polistirex and chlorpheniramine polistirex) extended-release capsule contains hydrocodone polistirex equivalent to 10 mg of hydrocodone bitartrate and chlorpheniramine polistirex equivalent to 8 mg of chlorpheniramine maleate. Each half-strength TussiCaps® (hydrocodone polistirex and chlorpheniramine polistirex) extended-release capsule contains hydrocodone polistirex equivalent to 5 mg of hydrocodone bitartrate and chlorpheniramine polistirex equivalent to 4 mg of chlorpheniramine maleate. TussiCaps® extended-release capsules provide up to 12-hour relief per dose. Hydrocodone is a centrally-acting narcotic antitussive. Chlorpheniramine is an antihistamine. TussiCaps® extended-release capsules are for oral use only.

Hydrocodone Polistirex: sulfonated styrene-divinylbenzene copolymer complex with 4,5α-epoxy-3-methoxy-17-methylmorphinan-6-one.

Chlorpheniramine Polistirex: sulfonated styrene-divinylbenzene copolymer complex with 2-[p-chloro-α-[2-(dimethylamino)ethyl]-benzyl]pyridine.

Inactive Ingredients: Butyl alcohol, dehydrated alcohol, gelatin, iron oxide black JPE, isopropyl alcohol, microcrystalline cellulose, propylene glycol, purified water, SDA 3A alcohol (27 CFR), shellac, shellac glaze-45% in SD-45 alcohol, strong ammonia solution, titanium dioxide, D&C yellow #10, D&C yellow #10 aluminum lake, FD&C blue #1/brilliant blue FCF aluminum lake, FD&C blue #2 aluminum lake, FD&C blue #2/indigo carmine aluminum lake, and FD&C red #40/allura red AC aluminum lake.

CLINICAL PHARMACOLOGY

Hydrocodone is a semisynthetic narcotic antitussive and analgesic with multiple actions qualitatively similar to those of codeine. The precise mechanism of action of hydrocodone and other opiates is not known; however, hydrocodone is believed to act directly on the cough center. In excessive doses, hydrocodone, like other opium derivatives, will depress respiration. The effects of hydrocodone in therapeutic doses on the cardiovascular system are insignificant. Hydrocodone can produce miosis, euphoria, and physical and psychological dependence.

Chlorpheniramine is an antihistamine drug (H1 receptor antagonist) that also possesses anticholinergic and sedative activity. It prevents released histamine from dilating capillaries and causing edema of the respiratory mucosa.

Hydrocodone and chlorpheniramine release from TussiCaps® extended-release capsules is controlled by use of an ion-exchange polymer matrix.

Following multiple dosing with hydrocodone polistirex and chlorpheniramine polistirex extended-release suspension, hydrocodone mean (S.D.) peak plasma concentrations of 22.8 (5.9) ng/mL occurred at 3.4 hours. Chlorpheniramine mean (S.D.) peak plasma concentrations of 58.4 (14.7) ng/mL occurred at 6.3 hours following multiple dosing. Peak plasma levels obtained with an immediate-release syrup occurred at approximately 1.5 hours for hydrocodone and 2.8 hours for chlorpheniramine. The plasma half-lives of hydrocodone and chlorpheniramine have been reported to be approximately 4 and 16 hours, respectively.

INDICATIONS AND USAGE

TussiCaps® (hydrocodone polistirex and chlorpheniramine polistirex) extended-release capsules are indicated for relief of cough and upper respiratory symptoms associated with allergy or a cold in adults and children 6 years of age and older.

CONTRAINDICATIONS

TussiCaps® extended-release capsules are contraindicated in patients with a known allergy or sensitivity to hydrocodone or chlorpheniramine.

The use of TussiCaps® extended-release capsules are contraindicated in children less than 6 years of age due to the risk of fatal respiratory depression.

WARNINGS

Respiratory Depression – As with all narcotics, TussiCaps® extended-release capsules produce dose-related respiratory depression by directly acting on brain stem respiratory centers. Hydrocodone affects the center that controls respiratory rhythm, and may produce irregular and periodic breathing. Caution should be exercised when TussiCaps® extended-release capsules are used postoperatively and in patients with pulmonary disease, or whenever ventilatory function is depressed. If respiratory depression occurs, it may be antagonized by the use of naloxone hydrochloride and other supportive measures when indicated (see OVERDOSAGE).

Head Injury and Increased Intracranial Pressure – The respiratory depressant effects of narcotics and their capacity to elevate cerebrospinal fluid pressure may be markedly exaggerated in the presence of head injury, other intracranial lesions, or a pre-existing increase in intracranial pressure. Furthermore, narcotics produce adverse reactions, which may obscure the clinical course of patients with head injuries.

Acute Abdominal Conditions – The administration of narcotics may obscure the diagnosis or clinical course of patients with acute abdominal conditions.

Obstructive Bowel Disease – Chronic use of narcotics may result in obstructive bowel disease especially in patients with underlying intestinal motility disorder.

Pediatric Use – The use of TussiCaps® extended-release capsules are contraindicated in children less than 6 years of age (see CONTRAINDICATIONS).

In pediatric patients, as well as adults, the respiratory center is sensitive to the depressant action of narcotic cough suppressants in a dose-dependent manner. Caution should be exercised when administering TussiCaps® extended-release capsules to pediatric patients 6 years of age and older. Overdose or concomitant administration of TussiCaps® extended-release capsules with other respiratory depressants may increase the risk of respiratory depression in pediatric patients. Benefit to risk ratio should be carefully considered, especially in pediatric patients with respiratory embarrassment (e.g., croup) (see PRECAUTIONS).

PRECAUTIONS

General

Caution is advised when prescribing this drug to patients with narrow-angle glaucoma, asthma, or prostatic hypertrophy.

Special Risk Patients – As with any narcotic agent, TussiCaps® extended-release capsules should be used with caution in elderly or debilitated patients and those with severe impairment of hepatic or renal function, hypothyroidism, Addison's disease, prostatic hypertrophy, or urethral stricture. The usual precautions should be observed and the possibility of respiratory depression should be kept in mind.

Information for Patients

As with all narcotics, TussiCaps® extended-release capsules may produce marked drowsiness and impair the mental and/or physical abilities required for the performance of potentially hazardous tasks such as driving a car or operating machinery; patients should be cautioned accordingly. TussiCaps® extended-release capsules must not be diluted with fluids or mixed with other drugs as this may alter the resin-binding and change the absorption rate, possibly increasing the toxicity.

Keep out of the reach of children.

Cough Reflex – Hydrocodone suppresses the cough reflex; as with all narcotics, caution should be exercised when TussiCaps® extended-release capsules are used postoperatively, and in patients with pulmonary disease.

Drug Interactions

Patients receiving narcotics, antihistamines, antipsychotics, antianxiety agents, or other CNS depressants (including alcohol) concomitantly with TussiCaps® extended-release capsules may exhibit an additive CNS depression. When combined therapy is contemplated, the dose of one or both agents should be reduced.

The use of MAO inhibitors or tricyclic antidepressants with hydrocodone preparations may increase the effect of either the antidepressant or hydrocodone.

The concurrent use of other anticholinergics with hydrocodone may produce paralytic ileus.

Carcinogenesis, Mutagenesis, Impairment of Fertility

Carcinogenicity, mutagenicity and reproductive studies have not been conducted with TussiCaps® extended-release capsules.

Pregnancy

TERATOGENIC EFFECTS

Teratogenic Effects. Pregnancy Category C – Hydrocodone has been shown to be teratogenic in hamsters when given in doses 700 times the human dose. There are no adequate and well-controlled studies in pregnant women. TussiCaps® extended-release capsules should be used during pregnancy only if the potential benefit justifies the potential risk to the fetus.

NONTERATOGENIC EFFECTS

Nonteratogenic Effects – Babies born to mothers who have been taking opioids regularly prior to delivery will be physically dependent. The withdrawal signs include irritability and excessive crying, tremors, hyperactive reflexes, increased respiratory rate, increased stools, sneezing, yawning, vomiting, and fever. The intensity of the syndrome does not always correlate with the duration of maternal opioid use or dose.

Labor and Delivery

As with all narcotics, administration of TussiCaps® extended-release capsules to the mother shortly before delivery may result in some degree of respiratory depression in the newborn, especially if higher doses are used.

Nursing Mothers

It is not known whether this drug is excreted in human milk. Because many drugs are excreted in human milk and because of the potential for serious adverse reactions in nursing infants from TussiCaps® extended-release capsules, a decision should be made whether to discontinue nursing or to discontinue the drug, taking into account the importance of the drug to the mother.

Pediatric Use

The use of TussiCaps® extended-release capsules are contraindicated in children less than 6 years of age (see CONTRAINDICATIONS and ADVERSE REACTIONS, Respiratory, Thoracic and Mediastinal Disorders).

TussiCaps® extended-release capsules should be used with caution in pediatric patients 6 years of age and older (see WARNINGS, Pediatric Use).

Geriatric Use

Clinical studies of hydrocodone polistirex and chlorpheniramine polistirex extended-release did not include sufficient numbers of subjects aged 65 and over to determine whether they respond differently from younger subjects. Other reported clinical experience has not identified differences in responses between the elderly and younger patients. In general, dose selection for an elderly patient should be cautious, usually starting at the low end of the dosing range, reflecting the greater frequency of decreased hepatic, renal, or cardiac function, and of concomitant disease or other drug therapy.

This drug is known to be substantially excreted by the kidney, and the risk of toxic reactions to this drug may be greater in patients with impaired renal function. Because elderly patients are more likely to have decreased renal function, care should be taken in dose selection, and it may be useful to monitor renal function.

ADVERSE REACTIONS

Gastrointestinal Disorders

Nausea and vomiting may occur; they are more frequent in ambulatory than in recumbent patients. Prolonged administration of TussiCaps® extended-release capsules may produce constipation.

General Disorders and Administration Site Conditions

Death

Nervous System Disorders

Sedation, drowsiness, mental clouding, lethargy, impairment of mental and physical performance, anxiety, fear, dysphoria, euphoria, dizziness, psychic dependence, mood changes.

Renal and Urinary Disorders

Ureteral spasm, spasm of vesical sphincters, and urinary retention have been reported with opiates.

Respiratory, Thoracic and Mediastinal Disorders

Dryness of the pharynx, occasional tightness of the chest, and respiratory depression (see CONTRAINDICATIONS).

TussiCaps® extended-release capsules may produce dose-related respiratory depression by acting directly on brain stem respiratory centers (see OVERDOSAGE). Use of TussiCaps® extended-release capsules in children less than 6 years of age has been associated with fatal respiratory depression. Overdose with TussiCaps® extended-release capsules in children 6 years of age and older, in adolescents, and in adults has been associated with fatal respiratory depression.

Skin and Subcutaneous Tissue Disorders

Rash, pruritus.

DRUG ABUSE AND DEPENDENCE

TussiCaps® extended-release capsules are Schedule III narcotics. Psychic dependence, physical dependence and tolerance may develop upon repeated administration of narcotics; therefore, TussiCaps® extended-release capsules should be prescribed and administered with caution. However, psychic dependence is unlikely to develop when TussiCaps® extended-release capsules are used for a short time for the treatment of cough. Physical dependence, the condition in which continued administration of the drug is required to prevent the appearance of a withdrawal syndrome, assumes clinically significant proportions only after several weeks of continued oral narcotic use, although some mild degree of physical dependence may develop after a few days of narcotic therapy.

OVERDOSAGE

Signs and Symptoms – Serious overdosage with hydrocodone is characterized by respiratory depression (a decrease in respiratory rate and/or tidal volume, Cheyne-Stokes respiration, cyanosis), extreme somnolence progressing to stupor or coma, skeletal muscle flaccidity, cold and clammy skin, and sometimes bradycardia and hypotension. Although miosis is characteristic of narcotic overdose, mydriasis may occur in terminal narcosis or severe hypoxia. In severe overdosage, apnea, circulatory collapse, cardiac arrest and death may occur. The manifestations of chlorpheniramine overdosage may vary from central nervous system depression to stimulation.

Treatment – Primary attention should be given to the reestablishment of adequate respiratory exchange through provision of a patent airway and the institution of assisted or controlled ventilation. The narcotic antagonist naloxone hydrochloride is a specific antidote for respiratory depression which may result from overdosage or unusual sensitivity to narcotics including hydrocodone. Therefore, an appropriate dose of naloxone hydrochloride should be administered, preferably by the intravenous route, simultaneously with efforts at respiratory resuscitation. Since the duration of action of hydrocodone in this formulation may exceed that of the antagonist, the patient should be kept under continued surveillance and repeated doses of the antagonist should be administered as needed to maintain adequate respiration. For further information, see full prescribing information for naloxone hydrochloride. An antagonist should not be administered in the absence of clinically significant respiratory depression. Oxygen, intravenous fluids, vasopressors and other supportive measures should be employed as indicated. Gastric emptying may be useful in removing unabsorbed drug.

DOSAGE AND ADMINISTRATION

Adults and Children 12 Years and Older

One (1) full-strength TussiCaps® extended-release capsule (hydrocodone polistirex equivalent to 10 mg of hydrocodone bitartrate and chlorpheniramine polistirex equivalent to 8 mg of chlorpheniramine maleate) every 12 hours; do not exceed 2 capsules in 24 hours.

Children 6 to 11 Years of Age

One (1) half-strength TussiCaps® extended-release capsule (hydrocodone polistirex equivalent to 5 mg of hydrocodone bitartrate and chlorpheniramine polistirex equivalent to 4 mg of chlorpheniramine maleate) every 12 hours; do not exceed 2 capsules in 24 hours.

This medicine is contraindicated in children under 6 years of age (see CONTRAINDICATIONS).

HOW SUPPLIED

Full-Strength: 10 mg/8 mg

TussiCaps® (hydrocodone polistirex and chlorpheniramine polistirex) extended-release capsules

Each full-strength capsule contains hydrocodone polistirex equivalent to 10 mg hydrocodone bitartrate and chlorpheniramine polistirex equivalent to 8 mg chlorpheniramine maleate. It is available as an Ivory/Ivory capsule printed in blue with “” on the cap and “HP/CP” over “10/8” on the body.

Bottles of 20.......................................NDC 54868-5957-0

STORAGE AND HANDLING

Storage: Store at 20° to 25°C (68° to 77°F) [see USP Controlled Room Temperature].

Dispense in a well-closed container.

A Schedule CIII Narcotic.

For Medical Information

Contact: Product Monitoring Department
Phone: 800-778-7898

Manufactured by:
Mallinckrodt Inc.
Hazelwood, Missouri
63042 U.S.A.

COVIDIEN, COVIDIEN with Logo, TussiCaps and are trademarks of Covidien AG or an affiliate.

© 2008 Covidien AG or an affiliate. All rights reserved.

Rev 060308

COVIDIEN
Mallinckrodt

Additional barcode labeling by:

Physicians Total Care, Inc.

Tulsa, Oklahoma 74146

PACKAGE LABEL - PRINCIPAL DISPLAY PANEL - 10 mg/8 mg Bottle

NDC 54868-5957-0
20 CAPSULES
TussiCaps®
(Hydrocodone Polistirex and Chlorpheniramine Polistirex)
Extended-Release Capsules
CIII
10 mg/8 mg (full-strength)
Contraindicated in children under 6 years of age.
Each capsule contains:
Hydrocodone Polistirex equivalent to 10 mg hydrocodone bitartrate
Chlorpheniramine Polistirex equivalent to 8 mg chlorpheniramine maleate
Rx only
This package is not for household use.